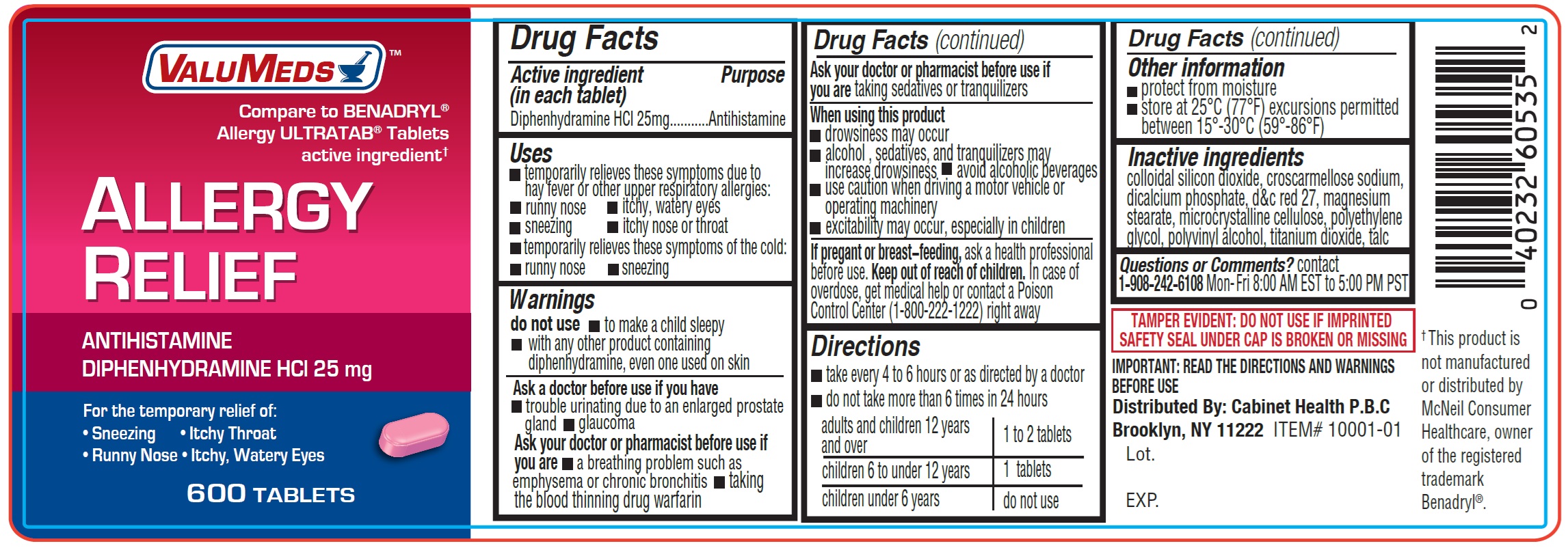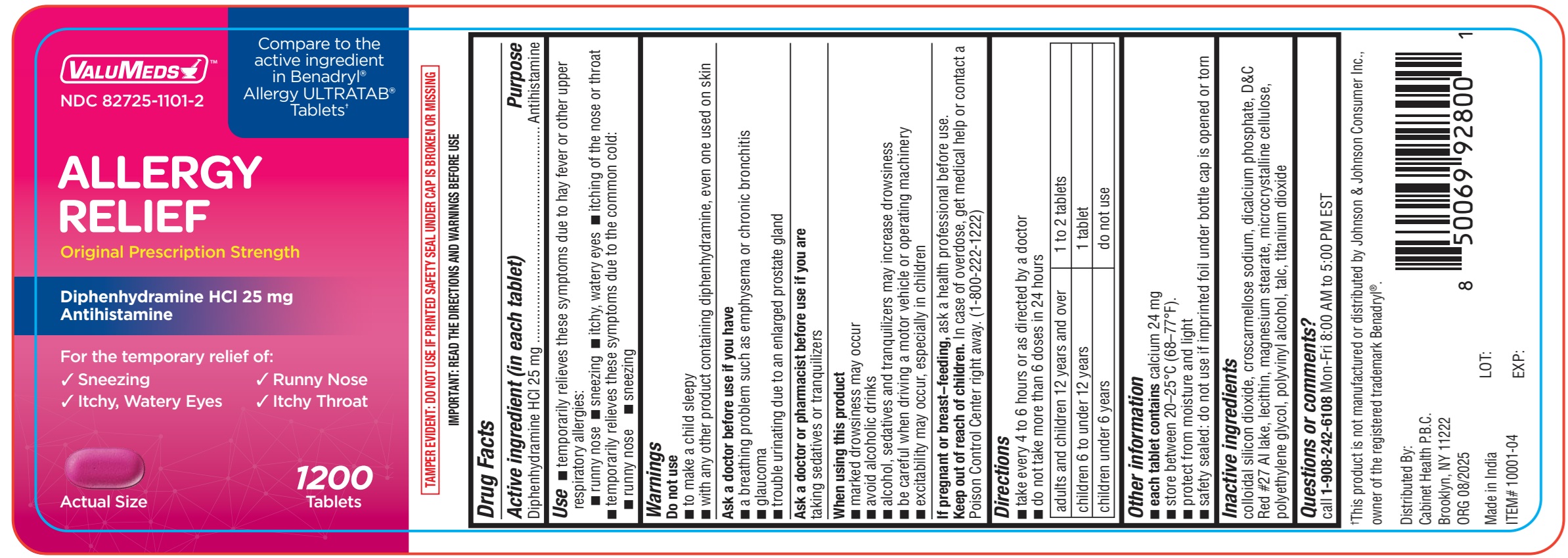 DRUG LABEL: ValuMeds Allergy Relief Antihistamine Diphenhydramine HCl
NDC: 82725-1101 | Form: TABLET
Manufacturer: Cabinet Health P.B.C.
Category: otc | Type: HUMAN OTC DRUG LABEL
Date: 20251229

ACTIVE INGREDIENTS: DIPHENHYDRAMINE HYDROCHLORIDE 25 mg/1 1
INACTIVE INGREDIENTS: CROSCARMELLOSE SODIUM; DICALCIUM PHOSPHATE; D&C RED NO. 27; MAGNESIUM STEARATE; MICROCRYSTALLINE CELLULOSE; POLYETHYLENE GLYCOL, UNSPECIFIED; POLYVINYL ALCOHOL; TITANIUM DIOXIDE; TALC; SILICON DIOXIDE

ValuMeds Allergy Relief Antihistamine Diphenhydramine HCl

Active ingredient (in each tablet)

Diphenhydramine HCl 25mg

Purpose

Antihistamine

Uses

- temporarily relieves these symptoms due to hay fever or other upper respiratory allergies:
- runny nose
- itchy, watery eyes
- sneezing
- itchy nose or throat
- temporarily relieves these symptoms of the cold:
- runny nose
- sneezing

Warnings

do not use

- to make a child sleepy
- with any other product containing diphenhydramine, even one used on skin

Ask a doctor before use if you have

- trouble urinating due to an enlarged prostate gland
- glaucoma

Ask your doctor or pharmacist before use if you are

- a breathing problem such as emphysema or chronic bronchitis
- taking the blood thinning drug warfarin

Ask your doctor or pharmacist before use if you are

taking sedatives or tranquilizers

When using this product

- drowsiness may occur
- alcohol, sedatives, and tranquilizers may increase drowsiness.
- avoid alcoholic beverages
- use caution when driving a motor vehicle or operating machinery
- excitability may occur, especially in children

If pregnant or breast-feeding,

ask a health professional before use.

Keep out of reach of children.

In case of overdose, get medical help or contact a Poison Control Center (1-800-222-1222) right away

Directions

- take every 4 to 6 hours or as directed by a doctor
- do not take more than 6 doses in 24 hours

adults and children 12 years and over | 1 to 2 tablets
children 6 to under 12 years | 1 tablet
children under 6 years | do not use

Other information

- protect from moisture
- store at 25°C (77°F) excursions permitted between 15°-30°C (59°-86°F)

Inactive ingredients

colloidal silicon dioxide, croscarmellose sodium, dicalcium phosphate, d&c red 27, magnesium stearate, microcrystalline cellulose, polyethylene glycol, polyvinyl alcohol, titanium dioxide, talc

Questions or Comments?

contact 1-908-242-6108 Mon- Fri 8:00 AM EST to 5:00 PM PST